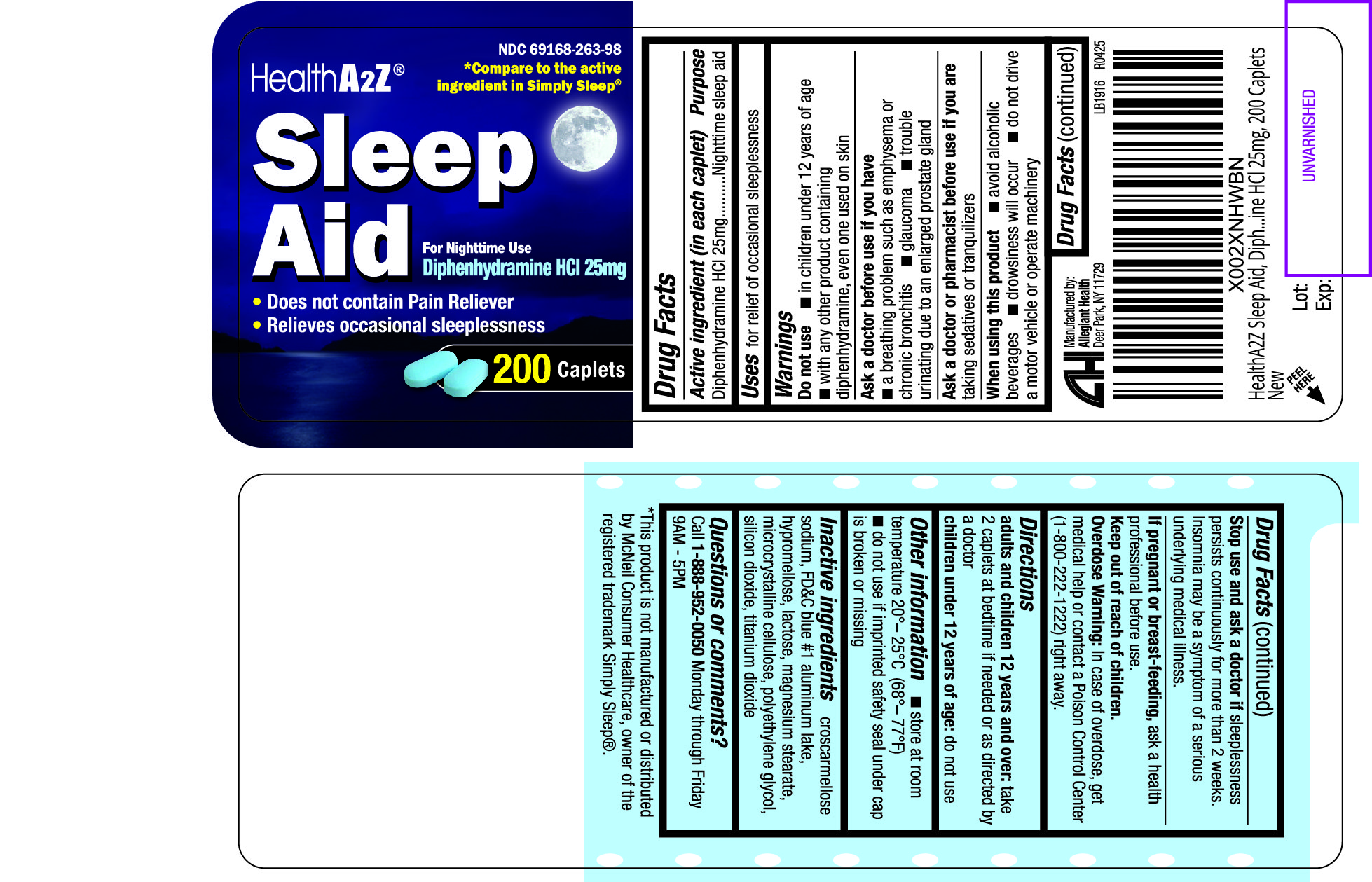 DRUG LABEL: Sleep Aid
NDC: 69168-263 | Form: TABLET
Manufacturer: Allegiant Health
Category: otc | Type: HUMAN OTC DRUG LABEL
Date: 20181221

ACTIVE INGREDIENTS: DIPHENHYDRAMINE HYDROCHLORIDE 25 mg/1 1
INACTIVE INGREDIENTS: SILICON DIOXIDE; CROSCARMELLOSE SODIUM; FD&C BLUE NO. 1; HYPROMELLOSES; LACTOSE, UNSPECIFIED FORM; MAGNESIUM STEARATE; CELLULOSE, MICROCRYSTALLINE; POLYETHYLENE GLYCOL, UNSPECIFIED; TITANIUM DIOXIDE

Drug Facts

Active ingredient (in each caplet)

Diphenhydramine HCl 25 mg

Purpose

Nighttime sleep aid

Uses

relief of occasional sleeplessness

Warnings

Do not use

- in children under 12 years of age
- with any other products containing diphenhydramine, including ones used on skin

Ask doctor before use if you have

- a breathing problem such as emphysema or chronic bronchitis
- glaucoma
- trouble urinating due to an enlarged prostate gland

Ask Doctor or Pharmacist before use if you

are taking sedatives or tranquilizers

When using this product

- avoid alcoholic beverages
- drowsiness may occur
- do not drive a motor vehicle or operating machinery

Stop use and ask a doctor if

sleeplessness persists continuously for more than 2 weeks. Insomnia may be a symptom of a serious underlying medical illness.

If pregnancy or breast-feeding

ask a health professional before use.

Keep Out of Reach of Children

In case of accidental overdose, contact a doctor or Poison Control Center (1-800-222-1222) right away.

Directions

adults and children 12 years and over: take 2 caplets at bedtime if needed or as directed by a doctor

children under 12 years of age: do not use

Other information

- store at room temperature store between 20-25°C (68-77°F)
- do not use if blister unit is torn or open

Inactive Ingredients

croscarmellose sodium, FD&C blue #1 aluminum lake, hypromellose, lactose, magnesium stearate, microcrystalline cellulose, polyethylene glycol, silicon dioxide, titanium dioxide

Package/Label Principal Display Panel

Sleep Aid